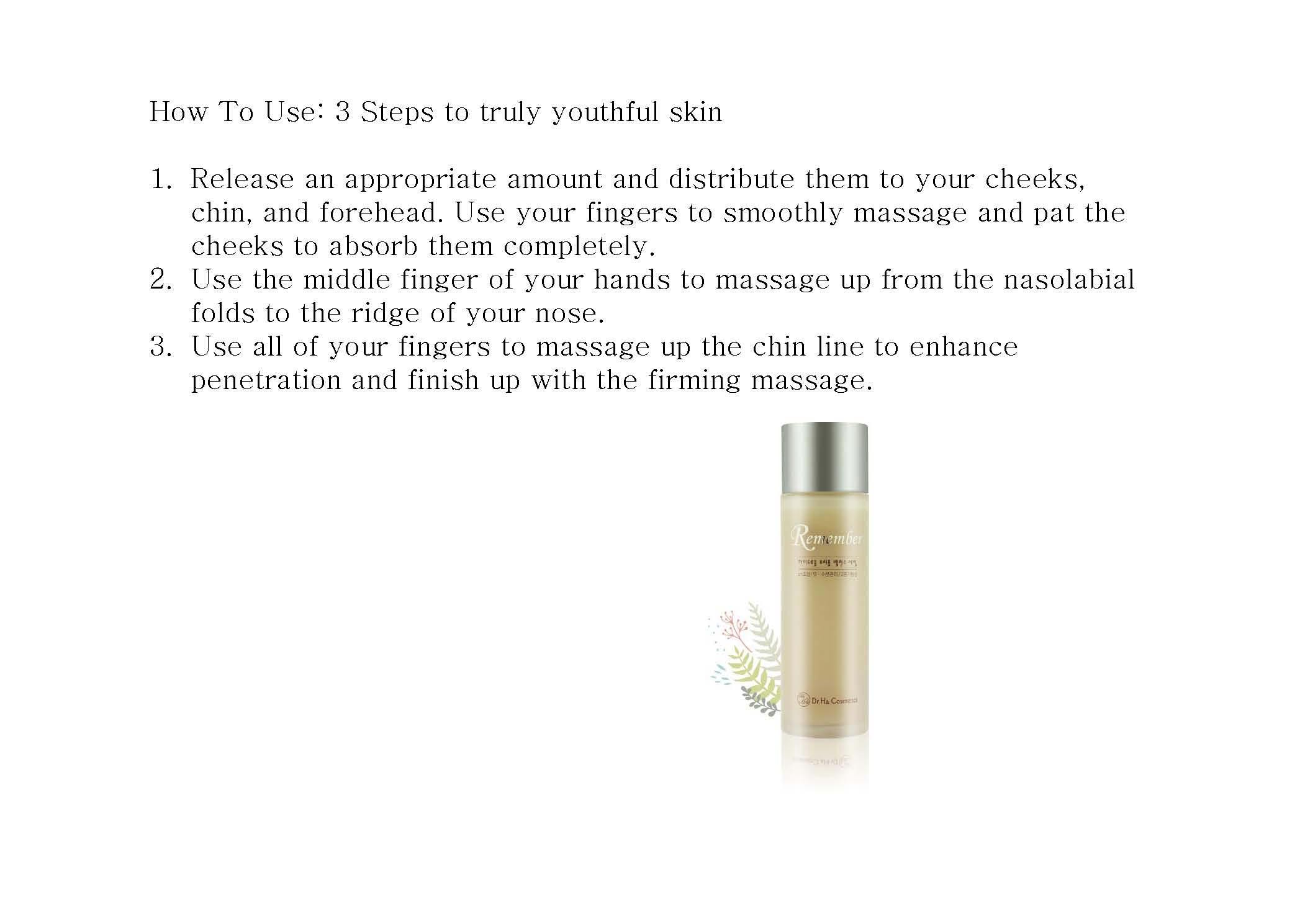 DRUG LABEL: REMEMBER SERUM
NDC: 69309-2001 | Form: LIQUID
Manufacturer: Dr. Ha Skin Lab Co.
Category: otc | Type: HUMAN OTC DRUG LABEL
Date: 20141022

ACTIVE INGREDIENTS: GLYCERIN 2 g/100 mL
INACTIVE INGREDIENTS: ADENOSINE; NIACINAMIDE

Drug Facts

ACTIVE INGREDIENT

glycerin

INACTIVE INGREDIENT

sorbitol, silica, adenosine, oriental herb ext, niacinamide, etc

PURPOSE

anti wrinkle
whitening
skin protectant

keep out or reach of the children

INDICATIONS AND USAGE

Release an appropriate amount and distribute them to your cheeks, chin, and forehead. Use your fingers to smoothly massage and pat the cheeks to absorb them completely.
Use the middle finger of your hands to massage up from the nasolabial folds to the ridge of your nose.
Use all of your fingers to massage up the chin line to enhance penetration and finish up with the firming massage

WARNINGS

- avoid direct sun exposure, keep it refrigerated or in cooler places
- do not eat

DOSAGE AND ADMINISTRATION

for exernal use only